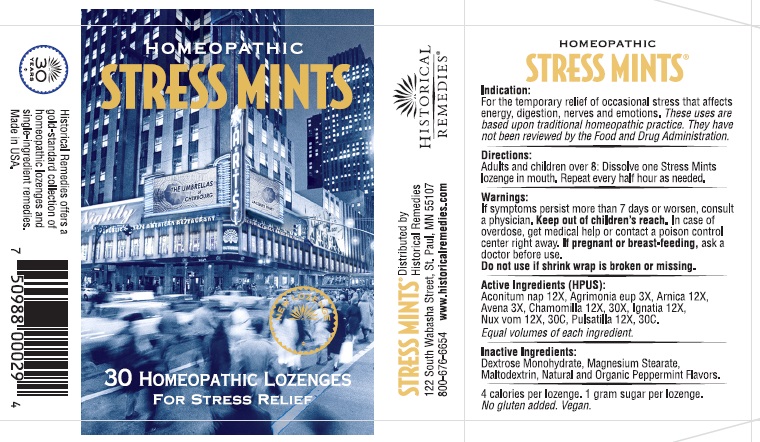 DRUG LABEL: Homeopathic Stress Mints
NDC: 57556-004 | Form: LOZENGE
Manufacturer: Historical Remedies LLP
Category: otc | Type: HUMAN OTC DRUG LABEL
Date: 20251007

ACTIVE INGREDIENTS: AGRIMONIA EUPATORIA 3 [hp_X]/1 1; MATRICARIA CHAMOMILLA WHOLE 12 [hp_X]/1 1; ARNICA MONTANA WHOLE 12 [hp_X]/1 1; PHOSPHORIC ACID 12 [hp_X]/1 1; AVENA SATIVA FLOWERING TOP 3 [hp_X]/1 1; STRYCHNOS IGNATII SEED 12 [hp_X]/1 1; PULSATILLA VULGARIS WHOLE 12 [hp_X]/1 1; ACONITUM NAPELLUS 12 [hp_X]/1 1; STRYCHNOS NUX-VOMICA SEED 12 [hp_X]/1 1
INACTIVE INGREDIENTS: MAGNESIUM STEARATE; MALTODEXTRIN; LEMON OIL; DEXTROSE MONOHYDRATE

Indication

For the temporary relief of occasional stress that affects energy, digestion, nerves and emotions. These uses are based upon traditional homeopathic practice. They have not been reviewed by the Food and Drug Administration.

Directions

Adults and children over 8: Dissolve one Stress Mints lozenge in mouth. Repeat every half hour as needed.

Warnings

If symptoms persist more than 7 days or worsen, consult a physician. Keep out of children’s reach.In case of overdose, get medical help or contact a poison control center right away. I f pregnant or breast-feeding, ask a doctor before use.
Do not use if shrink wrap is broken or missing.

Active Ingredients (HPUS)

Aconitum nap 12X, Agrimonia eup 3X, Arnica 12X, Avena 3X, Chamomilla 12X, Chamomilla 30X, Ignatia 12X, Nux vom 12X, Nux vom 30C, Pulsatilla 12X, Pulsatilla, 30C.

Inactive Ingredients

Dextrose Monohydrate, Magnesium Stearate, Maltodextrin, Natural and Organic Peppermint Flavors.
4 calories per lozenge. 1 gram sugar per lozenge.
No gluten added. Vegan.